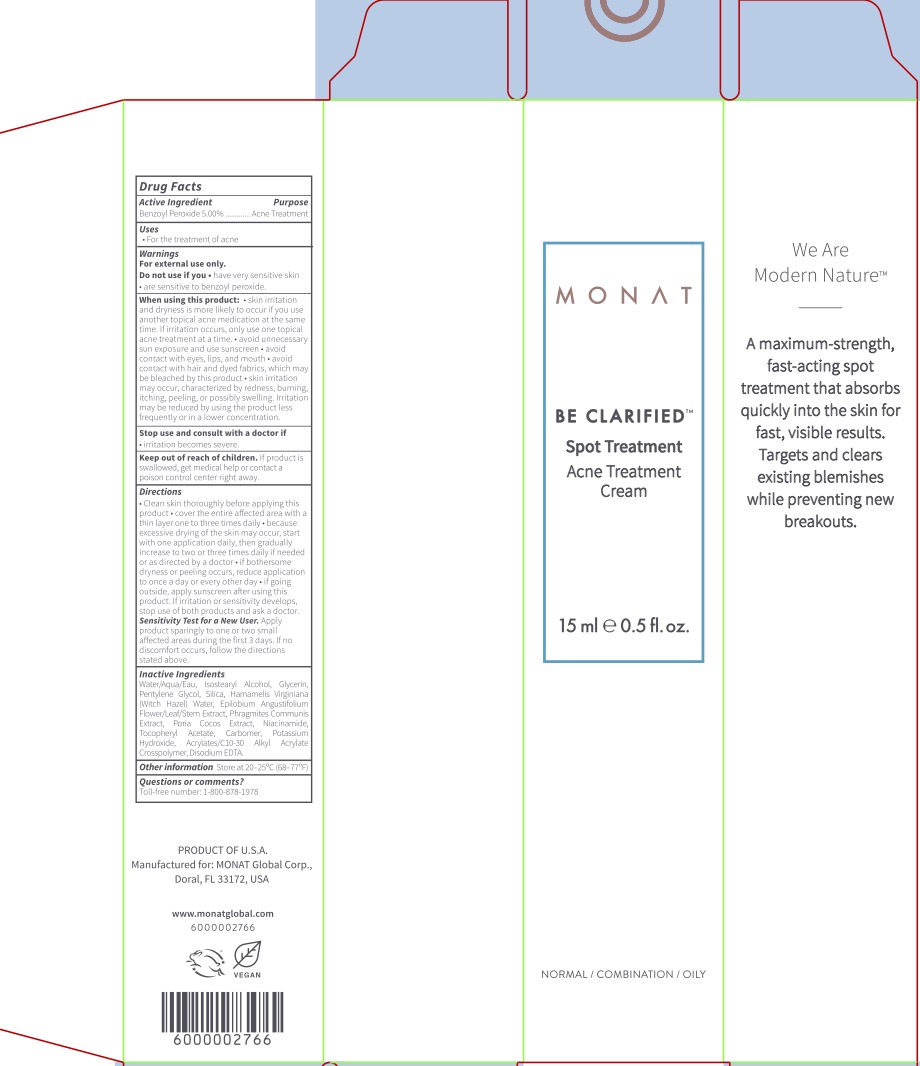 DRUG LABEL: Monat Acne Treatment
NDC: 78518-295 | Form: CREAM
Manufacturer: Monat Global Corp
Category: otc | Type: HUMAN OTC DRUG LABEL
Date: 20241220

ACTIVE INGREDIENTS: BENZOYL PEROXIDE 5 g/100 mL
INACTIVE INGREDIENTS: CARBOMER COPOLYMER TYPE A (ALLYL PENTAERYTHRITOL CROSSLINKED); ALPHA-TOCOPHEROL ACETATE; CARBOMER 940; POTASSIUM HYDROXIDE; NIACINAMIDE; HAMAMELIS VIRGINIANA TOP WATER; GLYCERIN; ISOSTEARYL ALCOHOL; PENTYLENE GLYCOL; EPILOBIUM ANGUSTIFOLIUM FLOWERING TOP; SILICON DIOXIDE; FU LING; WATER; PHRAGMITES AUSTRALIS STEM; EDETATE DISODIUM

ACTIVE INGREDIENT

Benzoyl Peroxide 5%

PURPOSE

Acne Treatment

INDICATIONS AND USAGE

For the treatment of acne.

Keep out of reach of children. If product is swallowed, get medical help or contact a Poison Control Center right away.

DOSAGE AND ADMINISTRATION

Clean skin thoroughly before applying this product. Cover the entire affected area with a thin layer one to three times daily. Because excessive drying of the skin may occur, start with one application daily, then gradually increase to two or three times daily if needed or as directed by a doctor. If bothersome dryness or peeling occurs, reduce application to once a day or every other day. If going outside, apply sunscreen after using this product. If irritation or sensitivity develops, stop use of both products and ask a doctor.

Sensitivity Test for a New User. Apply product sparingly to one or two small affected areas during the first 3 days. If no discomfort occurs, follow the directions stated above.

INACTIVE INGREDIENT

Water, Isostearyl Alcohol, Glycerin, Pentylene Glycol, Silica, Hamamelis Virginiana (Witch Hazel) Water, Epilobium Angustifolium Flower/Leaf/Stem Extract, Phragmites Communis Extract, Poria Cocos Extract, Niacinamide, Tocopheryl Acetate, Carbomer, Potassium Hydroxide, Acrylates/C10-30 Alkyl Acrylate Crosspolymer, Disodium EDTA.

WARNINGS

For external use only. Do not use if you have very sensitive skin or are sensitive to benzoyl peroxide. When using this product skin irritation and dryness is more likely to occur if you use another topical acne medication at the same time. If irritation occurs, only use one topical acne treatment at a time, avoid unnecessary sun exposure and use sunscreen, avoid contact with eyes, lips, and mouth, avoid contact with hair and dyed fabrics, which may be bleached by this product, skin irritation may occur, characterized by redness, burning, itching, peeling, or possibly swelling. Irritation may be reduced by using the product less frequently or in a lower concentration. Stop use and consult with a doctor if irritation becomes severe.